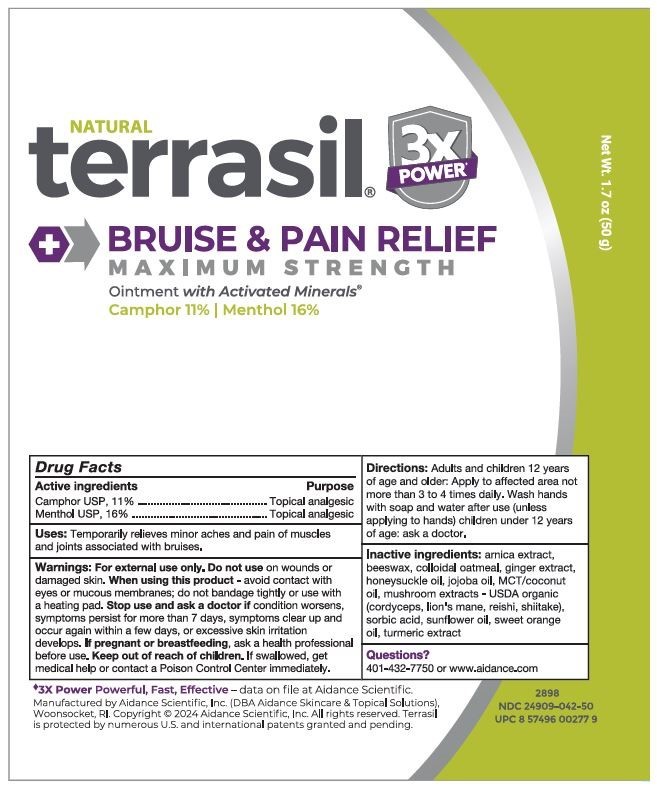 DRUG LABEL: terrasil Bruise and Pain Relief Maximum Strength
NDC: 24909-042 | Form: OINTMENT
Manufacturer: Aidance Scientific, Inc., DBA Aidance Skincare & Topical Solutions
Category: otc | Type: HUMAN OTC DRUG LABEL
Date: 20241009

ACTIVE INGREDIENTS: MENTHOL 16 g/100 g; CAMPHOR (NATURAL) 11 g/100 g
INACTIVE INGREDIENTS: ARNICA MONTANA FLOWER; YELLOW WAX; OATMEAL; GINGER; COCONUT OIL; AQUILEGIA CANADENSIS WHOLE; JOJOBA OIL; TURMERIC; OPHIOCORDYCEPS SINENSIS; HERICIUM ERINACEUS FRUITING BODY; REISHI; SHIITAKE MUSHROOM; SORBIC ACID; SUNFLOWER OIL; ORANGE OIL, COLD PRESSED

24909-042 terrasil Bruise & Pain Relief Maximum Strength

Active ingredients

Camphor USP, 11%, Menthol USP, 16%

Purpose

Topical analgesic

Uses

Temporarily relieves minor aches and pain of muscles and joints associated with bruises.

Warnings

For external use only.

Do not use on wounds or damaged skin.

When using this product avoid contact with eyes or mucous membranes; do not bandage tightly or use with a heating pad.

Stop use and ask a doctor if condition worsens symptoms persist for more than 7 days symptoms clear up and occur again within a few days excessive skin irritation develops.

PREGNANCY OR BREAST FEEDING

If pregnant or breastfeeding, ask a health professional before use.

Keep out of reach of children.

OTHER SAFETY INFORMATION

If swallowed, get medical help or contact a Poison Control Center immediately.

Directions

Adults and children 12 years of age and older: Apply to affected area not more than 3 to 4 times daily. Wash hands with soap and water after use (unless applying to hands) children under 12 years of age: ask a doctor.

Inactive ingredients

arnica extract, beeswax, colloidal oatmeal, ginger extract, honeysuckle oil, jojoba oil, MCT/coconut oil, mushroom extracts - USDA organic (cordyceps, lion's mane, reishi, shiitake), sorbic acid, sunflower oil, sweet orange oil, turmeric extract